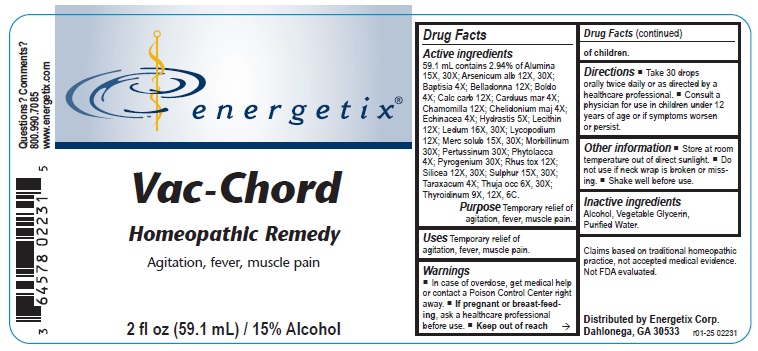 DRUG LABEL: Vac-Chord
NDC: 64578-0143 | Form: LIQUID
Manufacturer: Energetix Corporation
Category: homeopathic | Type: HUMAN OTC DRUG LABEL
Date: 20250711

ACTIVE INGREDIENTS: ALUMINUM OXIDE 15 [hp_X]/59.1 mL; ARSENIC TRIOXIDE 12 [hp_X]/59.1 mL; BAPTISIA TINCTORIA ROOT 4 [hp_X]/59.1 mL; ATROPA BELLADONNA 12 [hp_X]/59.1 mL; PEUMUS BOLDUS LEAF 4 [hp_X]/59.1 mL; OYSTER SHELL CALCIUM CARBONATE, CRUDE 12 [hp_X]/59.1 mL; MILK THISTLE 4 [hp_X]/59.1 mL; MATRICARIA RECUTITA 12 [hp_X]/59.1 mL; CHELIDONIUM MAJUS 4 [hp_X]/59.1 mL; ECHINACEA ANGUSTIFOLIA 4 [hp_X]/59.1 mL; GOLDENSEAL 5 [hp_X]/59.1 mL; EGG PHOSPHOLIPIDS 12 [hp_X]/59.1 mL; LEDUM PALUSTRE TWIG 16 [hp_X]/59.1 mL; LYCOPODIUM CLAVATUM SPORE 12 [hp_X]/59.1 mL; MERCURIUS SOLUBILIS 15 [hp_X]/59.1 mL; MEASLES VIRUS 30 [hp_X]/59.1 mL; HUMAN SPUTUM, BORDETELLA PERTUSSIS INFECTED 30 [hp_X]/59.1 mL; PHYTOLACCA AMERICANA ROOT 4 [hp_X]/59.1 mL; RANCID BEEF 30 [hp_X]/59.1 mL; TOXICODENDRON PUBESCENS LEAF 12 [hp_X]/59.1 mL; SILICON DIOXIDE 12 [hp_X]/59.1 mL; SULFUR 15 [hp_X]/59.1 mL; TARAXACUM OFFICINALE 4 [hp_X]/59.1 mL; THUJA OCCIDENTALIS LEAFY TWIG 6 [hp_X]/59.1 mL; THYROID, UNSPECIFIED 9 [hp_X]/59.1 mL
INACTIVE INGREDIENTS: ALCOHOL; GLYCERIN; WATER

Vac-Chord

ACTIVE INGREDIENT

Active ingredients59.1 mL contains 2.94% of: Alumina 15X, 30X; Arsenicum alb 12X, 30X; Baptisia 4X; Belladonna 12X; Boldo 4X; Calc carb 12X; Carduus mar 4X; Chamomilla 12X; Chelidonium maj 4X; Echinacea 4X; Hydrastis 5X; Lecithin 12X; Ledum 16X, 30X; Lycopodium 12X; Merc solub 15X, 30X; Morbillinum 30X; Pertussinum 30X; Phytolacca 4X; Pyrogenium 30X; Rhus tox 12X; Silicea 12X, 30X; Sulphur 15X, 30X; Taraxacum 4X; Thuja occ 6X, 30X; Thyroidinum 9X, 12X, 6C.

Claims based on traditional homeopathic practice, not accepted medical evidence. Not FDA evaluated.

Uses

Temporary relief of agitation, fever, muscle pain.

Warnings

- In case of overdose, get medical help or contact a Poison Control Center right away.
- If pregnant or breast feeding,ask a healthcare professional before use.

- Keep out of reach of children.

Directions

- Take 30 drops orally twice daily or as directed by a healthcare professional.
- Consult a physician for use in children under 12 years of age or if symptoms worsen or persist.

Other information

- Store at room temperature out of direct sunlight.
- Do not use if neck wrap is broken or missing.
- Shake well before use.

Inactive ingredients

Alcohol, Vegetable Glycerin, Purified Water.

QUESTIONS

Distributed by Energetix Corp.

Dahlonega, GA 30533

Questions? Comments?

800.990.7085

www.energetix.com

PACKAGE LABEL

energetix

Vac-Chord

Homeopathic Remedy

Agitation, fever, muscle pain

2 fl oz (59.1 mL) / 15% Alcohol

PURPOSE

PurposeTemporary relief of agitation, fever, muscle pain.